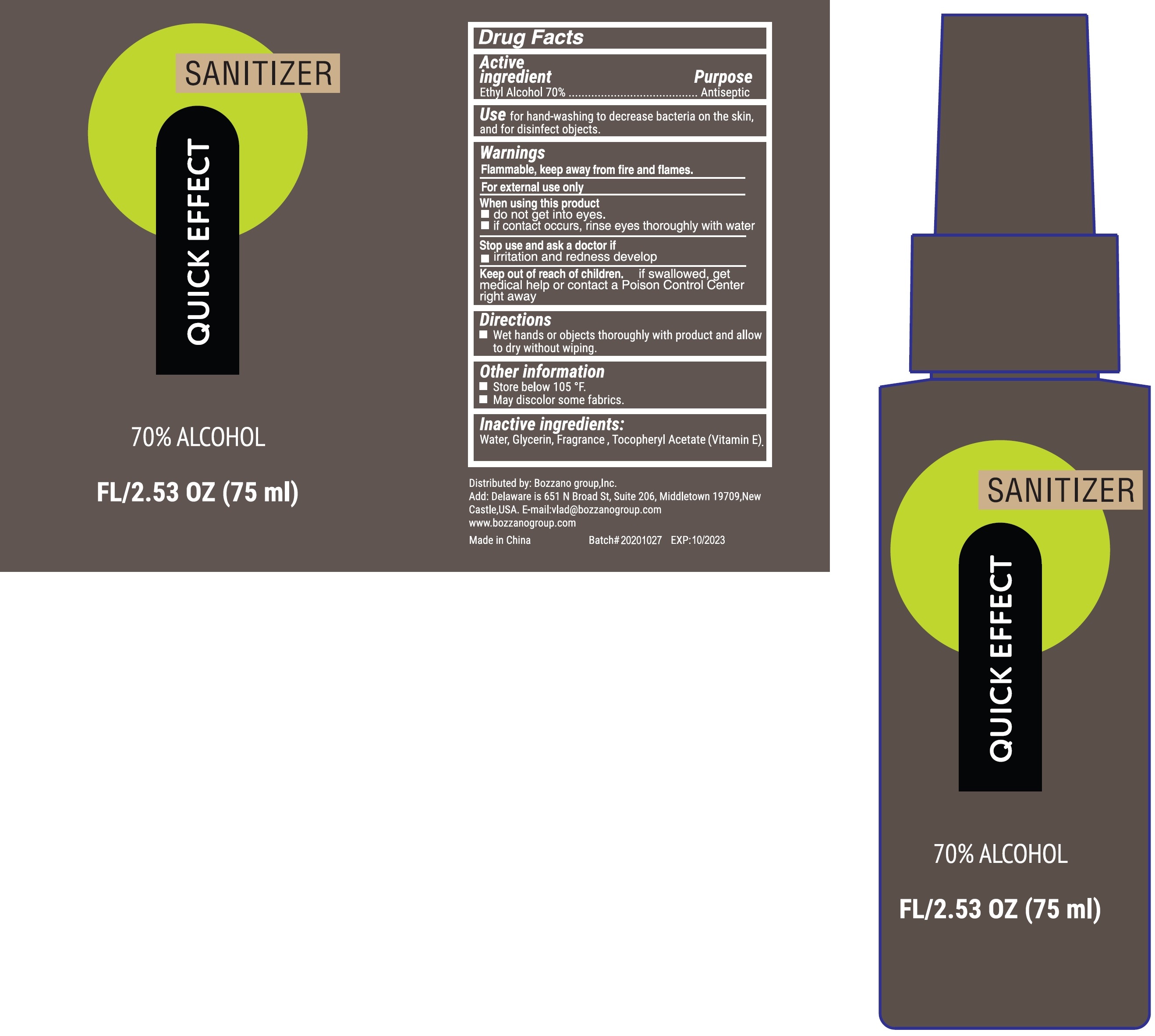 DRUG LABEL: SANITIZER
NDC: 79396-001 | Form: SPRAY
Manufacturer: BOZZANO Group
Category: otc | Type: HUMAN OTC DRUG LABEL
Date: 20231026

ACTIVE INGREDIENTS: ALCOHOL 0.7 mL/1 mL
INACTIVE INGREDIENTS: WATER; GLYCERIN; .ALPHA.-TOCOPHEROL ACETATE

SANITIZER

Active ingredient

Ethyl Alcohol 70%

Purpose

Antiseptic

Use

for hand-washing to decrease bacteria on the skin, and for disinfect objects.

Warnings

Flammable, keep away from fire and flames.

For external use only

When using this product

- do not get into eyes.
- if contact occurs, rinse eyes thoroughly with water

Stop use and ask a doctor if

- irritation and redness develop

Keep out of reach of children.

if swallowed, get medical help or contact a Poison Control Center right away

Directions

- Wet hands or objects thoroughly with product and allow to dry without wiping.

Other information

- Store below 105 °F.
- May discolor some fabrics.

Inactive ingredients:

Water, Glycerin, Fragrance, Tocopheryl Acetate (Vitamin E).